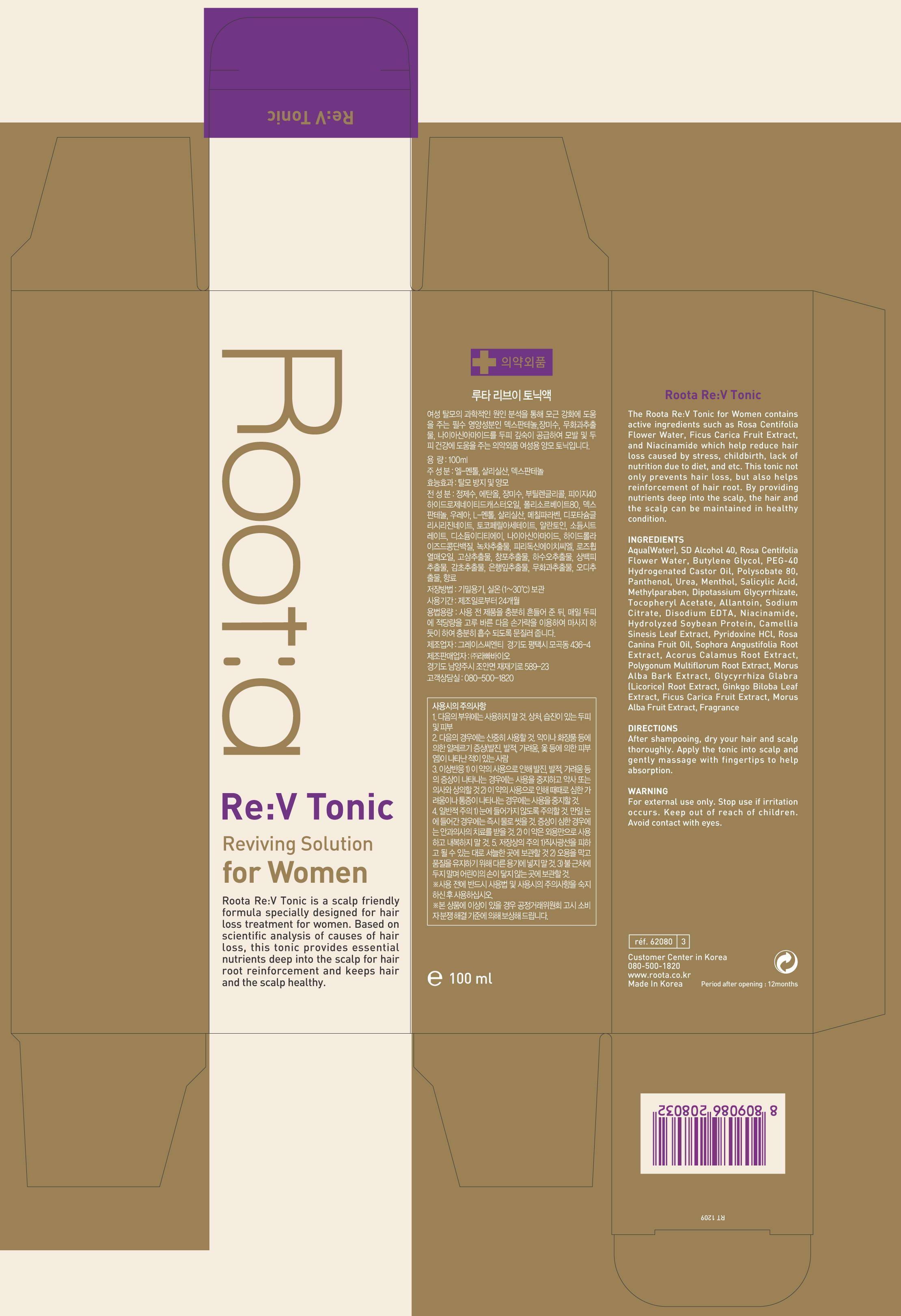 DRUG LABEL: Roota Re V Tonic
NDC: 54576-4001 | Form: LIQUID
Manufacturer: Raphabio Inc
Category: otc | Type: HUMAN OTC DRUG LABEL
Date: 20121231

ACTIVE INGREDIENTS: PANTHENOL 0.5 mg/100 mL
INACTIVE INGREDIENTS: WATER; ALCOHOL; BUTYLENE GLYCOL; POLYOXYL 40 HYDROGENATED CASTOR OIL; POLYSORBATE 80; UREA; MENTHOL; SALICYLIC ACID; ROSA CENTIFOLIA FLOWER; GLYCYRRHIZINATE DIPOTASSIUM; METHYLPARABEN; .ALPHA.-TOCOPHEROL ACETATE; SOY PROTEIN; ALLANTOIN; SODIUM CITRATE; ROSA CANINA FRUIT OIL; EDETATE DISODIUM; FICUS CARICA WHOLE; NIACINAMIDE; PYRIDOXINE HYDROCHLORIDE; SOPHORA FLAVESCENS ROOT; ACORUS CALAMUS ROOT; GINKGO; MORUS ALBA BARK; GLYCYRRHIZA GLABRA

Drug Facts

ACTIVE INGREDIENT

panthenol

INACTIVE INGREDIENT

Aqua (Water), rosa centifolia flower water, sd alcohol 40, butylene glycol, peg-40 hydrogenated castor oil, polysorbate 80, urea, menthol, salicylic acid, methylparaben, , dipotassium glycyrrhizate, hydrolyzed soybean protein, carmellia sinensis leaf extract, , allantoin, sodium citrate, zinc sulfate, disodium edta, rosemary leaf oil, niacinamide, panax ginseng root extract, pyridoxine hci, sophora angustifolia root extract, acorus calamus root extract, polygonum multiflorum root extract, morus alba bark extract, licorice root extract, ginkgo biloba leaf, ficus carica fruit extract, morus alba fruit extract, fragrance

PURPOSE

hair care

keep out of reach of the children

INDICATIONS AND USAGE

after shampooing, dry your hair and sclap thoroughly
apply the tonic into scalp and gently massage with fingertips to help absorption

stop use if irritation occurs

DOSAGE AND ADMINISTRATION

for external use only